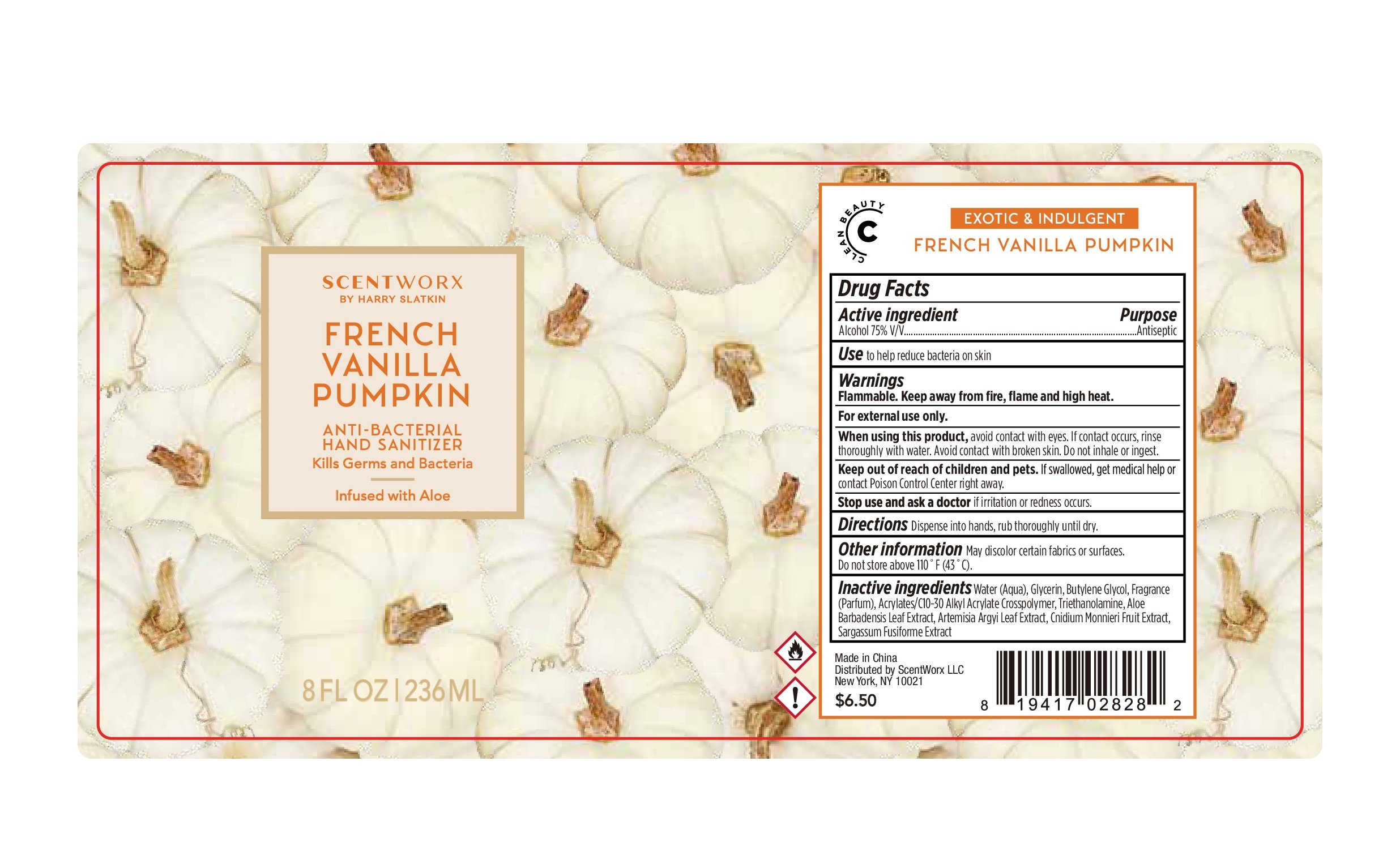 DRUG LABEL: ANTI-BACTERIAL HAND SANITIZER
NDC: 74620-039 | Form: GEL
Manufacturer: COSBE LABORATORY INC
Category: otc | Type: HUMAN OTC DRUG LABEL
Date: 20210224

ACTIVE INGREDIENTS: ALCOHOL 75 mL/100 mL
INACTIVE INGREDIENTS: TROLAMINE; CARBOMER INTERPOLYMER TYPE A (55000 CPS); FRAGRANCE CLEAN ORC0600327; SARGASSUM FUSIFORME; WATER; GLYCERIN; ALOE VERA LEAF; ARTEMISIA ARGYI LEAF; CNIDIUM MONNIERI FRUIT; BUTYLENE GLYCOL

74620-039
ANTI-BACTERIAL HAND SANITIZER

Active Ingredient

Alcohol 75% V/V

Purpose

Antiseptic

Use

Use to help reduce bacteria on skin

Warnings

Flammable. Keep away from fire, flame and high heat.
for external use only.

When using this product ,avoid contact with eyes. If contact occurs, rinse thoroughly with water. Avoid contact with brokern skin.
Do not inhale or ingest.

Keep out of reach of children and pets. If swallowed, get medical help or contact Poison Control Center right away.

Stop use and ask a doctor if irritation or redness occurs.

DO NOT USE

/

When using this product ,avoid contact with eyes. If contact occurs, rinse thoroughly with water. Avoid contact with brokern skin.
Do not inhale or ingest.

Keep out of reach of children and pets. If swallowed, get medical help or contact Poison Control Center right away.

Stop use and ask a doctor if irritation or redness occurs.

Stop use and ask a doctor if irritation or redness occurs.

Keep out of reach of children and pets. If swallowed, get medical help or contact Poison Control Center right away.

Directions

Dispense into hands, rub until dry.

Other information

May discolor certain fabrics or surfaces. Oo not stor above 110F (43C)

Inactive ingredients

Water(Aqua), Glycerin, Butylene Glycol, Fagrance(Parfum), Acrylates/C10-30Alkyl Acrylate Crosspolymer, Triethanolamine, Aloe Barbadensis Leaf Extract, Artemisia Argyi Leaf Extract, Cnidium Monnieri Frut Extrac, Sargassum Fusiforme Extract

PACKAGE LABEL

74620-039-01 236ml